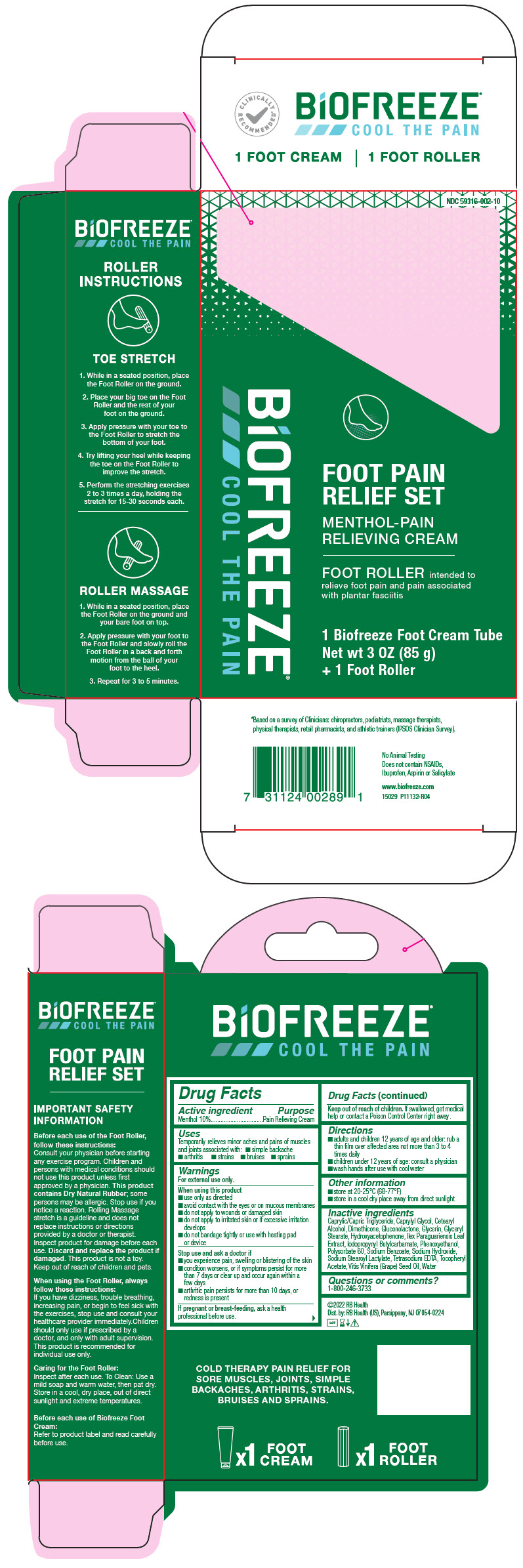 DRUG LABEL: Biofreeze Foot Pain Relief Set
NDC: 59316-002 | Form: KIT | Route: TOPICAL
Manufacturer: RB Health (US) LLC
Category: otc | Type: HUMAN OTC DRUG LABEL
Date: 20241227

ACTIVE INGREDIENTS: MENTHOL, UNSPECIFIED FORM 100 mg/1 g
INACTIVE INGREDIENTS: MEDIUM-CHAIN TRIGLYCERIDES; CAPRYLYL GLYCOL; CETOSTEARYL ALCOHOL; DIMETHICONE; GLUCONOLACTONE; GLYCERIN; GLYCERYL MONOSTEARATE; HYDROXYACETOPHENONE; ILEX PARAGUARIENSIS LEAF; IODOPROPYNYL BUTYLCARBAMATE; PHENOXYETHANOL; POLYSORBATE 60; SODIUM BENZOATE; SODIUM HYDROXIDE; SODIUM STEAROYL LACTYLATE; EDETATE SODIUM; .ALPHA.-TOCOPHEROL ACETATE; GRAPE SEED OIL; WATER

Biofreeze Foot Pain Relief Set

Active ingredient:

Menthol 10%

Purpose

Pain Relieving Cream

Uses:

Temporarily relieves minor aches and pains of muscles and joints associated with: • arthritis • simple backache • strains • sprains • bruises

Warnings

For external use only

When using this product:

- Use only as directed
- Avoid contact with the eyes or on mucous membranes
- Do not apply to wounds or damaged skin
- do not apply to irritated skin or if excessive irritation develops
- do not bandage tightly or use with heating pad or device

Stop use and ask a doctor if:

You experience pain, swelling or blistering of the skin; condition worsens, or if symptoms persist for more than 7 days, or clear up and occur again within a few days; arthritic pain persists for more than 10 days, or redness is present

If pregnant or breastfeeding:

Ask a health professional before use

Keep out of reach of children:

If accidentally ingested, get medical help or contact a Poison Control Center right away

Directions:

• Adults and Children 12 years of age and older: Rub a thin film over affected areas not more than 3 to 4 times daily;
• Children under 12 years of age: Consult a physician
• wash hands after use with cool water

Inactive ingredients:

Caprylic/Capric Triglyceride, Caprylyl Glycol, Cetearyl Alcohol, Dimethicone, Gluconolactone, Glycerin, Glyceryl Stearate, Hydroxyacetophenone, Ilex Paraguariensis Leaf Extract, Iodopropynyl Butylcarbamate, Phenoxyethanol, Polysorbate 60, Sodium Benzoate, Sodium Hydroxide, Sodium Stearoyl Lactylate, Tetrasodium EDTA, Tocopheryl Acetate, Vitis Vinifera (Grape) Seed Oil, Water

Questions or comments:

1-800-246-3733

PRINCIPAL DISPLAY PANEL - 85 g Tube Kit

NDC 59316-002-10

BiOFREEZE®
COOL THE PAIN

FOOT PAIN
RELIEF SET

MENTHOL-PAIN
RELIEVING CREAM

FOOT ROLLER intended to
relieve foot pain and pain associated
with plantar fasciitis

1 Biofreeze Foot Cream Tube
Net wt 3 OZ (85 g)
+ 1 Foot Roller